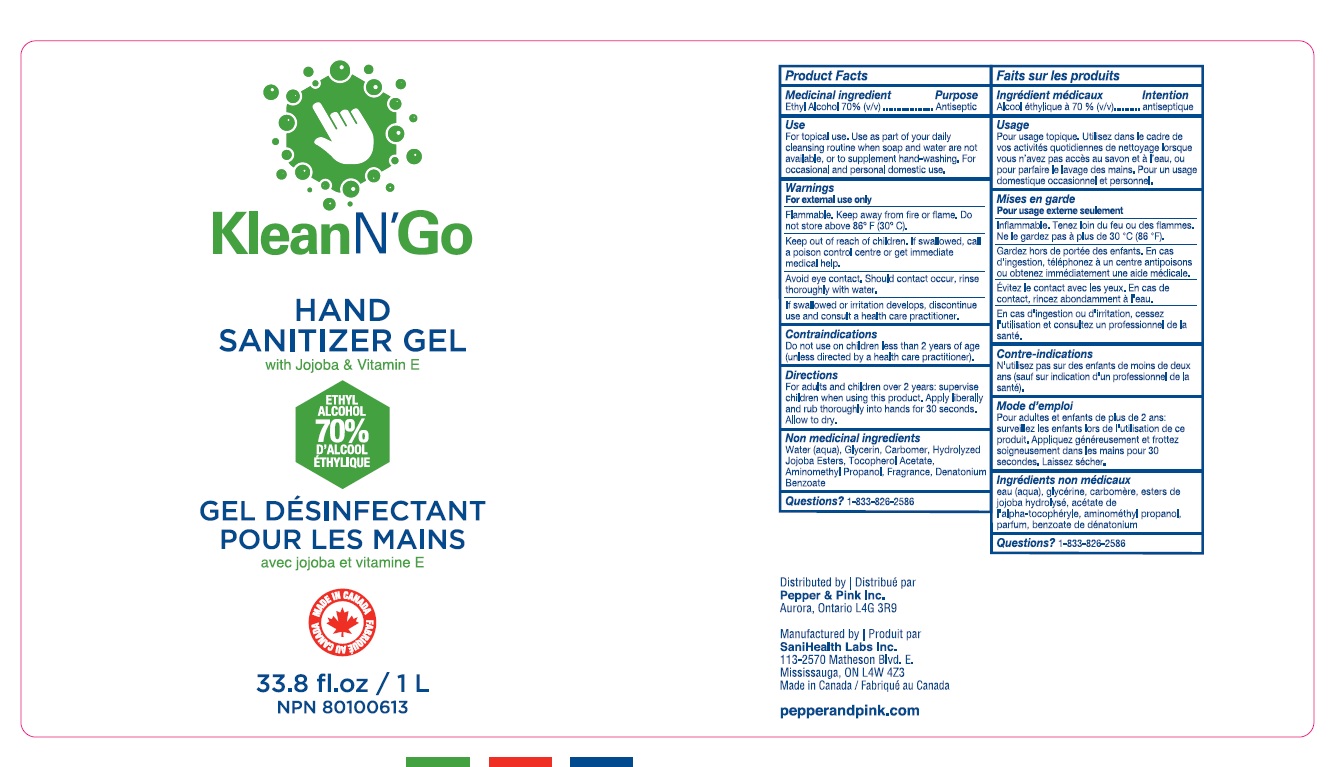 DRUG LABEL: KleanN Go Hand Sanitizer
NDC: 79861-002 | Form: GEL
Manufacturer: Sanihealth Labs Inc.
Category: otc | Type: HUMAN OTC DRUG LABEL
Date: 20210510

ACTIVE INGREDIENTS: ALCOHOL 0.7 mL/1 mL
INACTIVE INGREDIENTS: AMINOMETHYLPROPANOL; WATER; DENATONIUM BENZOATE; HYDROLYZED JOJOBA ESTERS (ACID FORM); CARBOMER HOMOPOLYMER TYPE C; GLYCERIN; ALPHA-TOCOPHEROL ACETATE

Klean N Go Hand Sanitizer

Active Ingredients

Ethyl Alcohol 70%v/v.

Purpose: Antiseptic

Purpose

Antiseptic

Uses

- For topical use. Use as part of your daily cleansing routine when soap and water are not available, or to supplement hand-washing. For occasional and personal domestic use.

Warnings

For external use only.

Flammable. Keep away from fire or flame.

Safety Instructions

Flammable, Keep away from fire and flame

Ask Doctor

Stop Use and Ask a doctor if irritation or redness develops

KEEP OUT OF REACH OF CHILDREN

If swallowed, get medical help or contact Poison Control right away

Directions

- For adults on children over 2 years: supervise children when using this product. Apply liberally and rub thoroughly into hand for 30 seconds. Allow to dry

Other Information

For Questions

Call- 1-833-826-2586

Inactive Ingredients

water, hydrolyzed jojoba esters, glycerin, carbopol, fragrance, aminomethyl propanol, denatonium benozate, tocopherol acetate